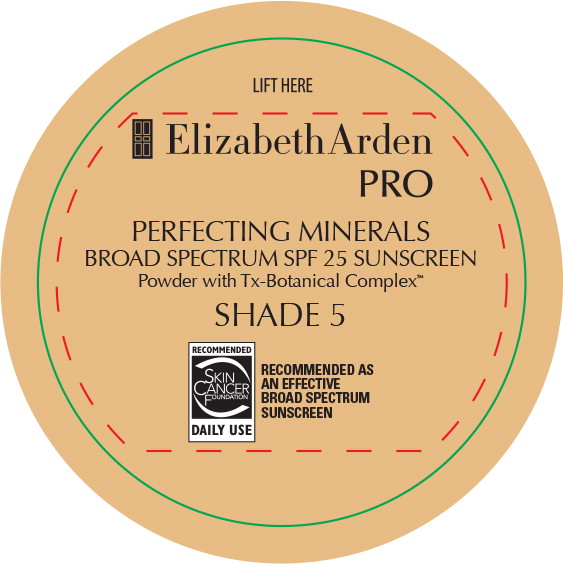 DRUG LABEL: PRO PERFECTING MINERALS BROAD SPECTRUM SPF 25 SUNSCREEN - SHADE 3
NDC: 67938-2081 | Form: LOTION
Manufacturer: ELIZABETH ARDEN, INC
Category: otc | Type: HUMAN OTC DRUG LABEL
Date: 20170201

ACTIVE INGREDIENTS: ZINC OXIDE 1 g/5 g
INACTIVE INGREDIENTS: MICA; GREEN TEA LEAF; VITIS VINIFERA SEED; COCOA; ACAI; TURMERIC; TITANIUM DIOXIDE; BISMUTH OXYCHLORIDE; FERRIC OXIDE YELLOW; FERRIC OXIDE RED; FERROSOFERRIC OXIDE

Drug Facts

Active Ingredients

Zinc Oxide 20%

Purpose

Sunscreen

Uses

- Helps prevent sunburn
- If used as directed with other sun protection measures (see Directions), decreases the risk of skin cancer and early skin aging caused by the sun

Warnings

- For external use only

- Do not use on damaged or broken skin

- When using this product keep out of eyes. Rinse with water to remove.

- Stop use and ask a doctor if rash occurs

- Keep out of reach of children. If product is swallowed, get medical help or contact a Poison Control Center right away.

Directions for Sunscreen Use:

- Apply liberally 15 minutes before sun exposure
- Reapply:
  - At least every 2 hours
  - Use a water resistant sunscreen if swimming or sweating
- Sun Protection Measures. Spending time in the sun increases your risk of skin cancer and early skin aging. To decrease this risk, regularly use a sunscreen with a broad spectrum SPF of 15 or higher and other sun protection measures including:
  - Limit time in the sun, especially from 10 a.m. – 2 p.m.
  - Wear long-sleeve shirts, pants, hats, and sunglasses
- Children under 6 months: Ask a doctor.

Inactive Ingredients

MICA, CAMELLIA SINENSIS LEAF EXTRACT, CHLOROGENIC ACIDS, CURCUMA LONGA (TURMERIC) ROOT EXTRACT, EUTERPE OLERACEA FRUIT EXTRACT, THEOBROMA CACAO (COCOA) SEED POWDER, VITIS VINIFERA (GRAPE) SEED EXTRACT [MAY CONTAIN/PEUT CONTENIR (+/-) BISMUTH OXYCHLORIDE (CI 77163), IRON OXIDES (CI 77491, CI 77492, CI 77499), TITANIUM DIOXIDE (CI 77891).

Other Information

- Protect this product from excessive heat and direct sun
- Store at room temperature

Questions or comments?

Call toll free 1-844-273-3679

Principal Display Panel - Jar Label

LIFT HERE

ElizabethArden

PRO

PERFECTING MINERALS

BROAD SPECTRUM SPF 25 SUNSCREEN

Powder with Tx-Botanical Complex™

SHADE 5

RECOMMENDED

SKIN
CANCER
FOUNDATION

DAILY USE

RECOMMENDED AS
AN EFFECTIVE
BROAD SPECTRUM
SUNSCREEN